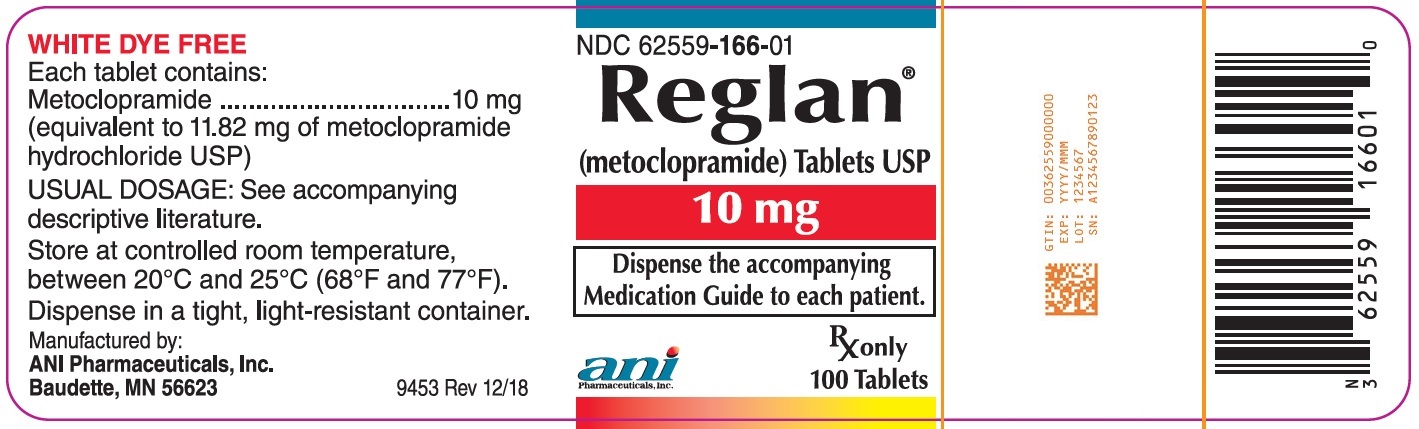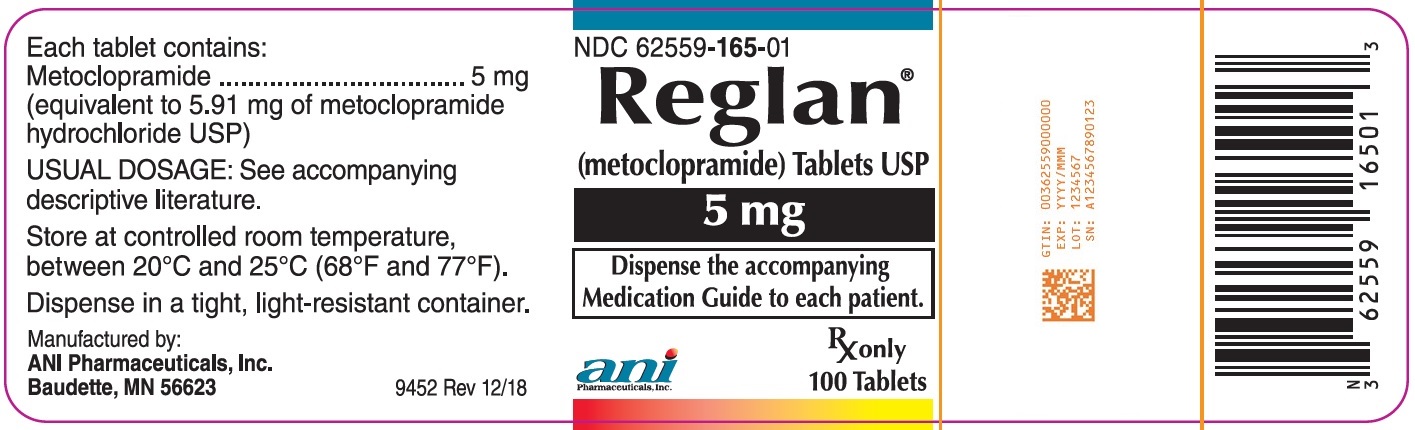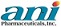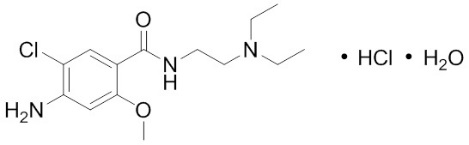 DRUG LABEL: Reglan
NDC: 62559-165 | Form: TABLET
Manufacturer: ANI Pharmaceuticals, Inc.
Category: prescription | Type: HUMAN PRESCRIPTION DRUG LABEL
Date: 20260209

ACTIVE INGREDIENTS: METOCLOPRAMIDE HYDROCHLORIDE 5 mg/1 1
INACTIVE INGREDIENTS: STARCH, CORN; SILICON DIOXIDE; MICROCRYSTALLINE CELLULOSE; STEARIC ACID; ANHYDROUS LACTOSE; D&C YELLOW NO. 10; FD&C BLUE NO. 1; ALUMINUM OXIDE

HIGHLIGHTS OF PRESCRIBING INFORMATION

These highlights do not include all the information needed to use REGLAN TABLETS safely and effectively. See full prescribing information for REGLAN TABLETS.
REGLAN® (metoclopramide) tablets, for oral use
Initial U.S. Approval: 1979

RECENT MAJOR CHANGES

Boxed Warning 02/2026

Indications and Usage (1) 02/2026

Dosage and Administration (2.1, 2.2) 02/2026

Warnings and Precautions, Tardive Dyskinesia (5.1) 02/2026

Warnings and Precautions, Other Extrapyramidal Symptoms (5.2) 02/2026

WARNING: TARDIVE DYSKINESIA

See full prescribing information for complete boxed warning.

- Metoclopramide, including Reglan, can cause tardive dyskinesia (TD), a potentially irreversible serious movement disorder In patients treated with metoclopramide, including Reglan, the risk of developing TD increases with duration of metoclopramide treatment and total cumulative metoclopramide dosage. (5.1)
- Reglan is contraindicated in patients with a history of TD. (4)
- Use Reglan for the shortest duration of treatment and periodically reassess the need for continued treatment. (2.1, 2.2, 5.1)
- Immediately discontinue Reglan in patients who develop signs or symptoms of TD. (5.1)
- In patients with symptomatic, documented gastroesophageal reflux, the maximum duration of treatment is 12 weeks. (2.1, 5.1)
- In patients with diabetic gastroparesis, avoid a total duration of treatment with metoclopramide products, including Reglan tablets, for longer than 12 weeks. If longer-term use is unavoidable, routinely monitor for signs and symptoms of TD. (5.1)

1 INDICATIONS AND USAGE

Reglan tablets are indicated for the:

- Treatment for 4 to 12 weeks of symptomatic, documented gastroesophageal reflux in adults who fail to respond to conventional therapy (1)
- Relief of symptoms in adults with acute and recurrent diabetic gastroparesis (1)

Limitations of Use:

- Reglan has not been shown to be safe and effective for the gastroesophageal reflux for longer than 12 weeks (1, 5.1).
- Reglan tablets are not recommended for use in pediatric patients due to the risk of tardive dyskinesia (TD) and other extrapyramidal symptoms as well as the risk of methemoglobinemia in neonates (1, 8.4)

2 DOSAGE AND ADMINISTRATION

Symptomatic, Documented Gastroesophageal Reflux in Adults Who Fail Conventional Therapy (2.1)

- Administer Reglan continuously or intermittently:

○ Continuous: The recommended dosage is 10 to 15 mg orally, 30 minutes before each meal and at bedtime (maximum of 60 mg per day) for 4 to 12 weeks, as determined by endoscopic response.

○ Intermittent: Single doses up to 20 mg prior to provoking situation.

Acute and Recurrent Diabetic Gastroparesis in Adults (2.2)

- The recommended dosage is 10 mg orally, 30 minutes before each meal and at bedtime (maximum of 40 mg per day).

Dosage Adjustment in Specific Populations (2.1, 2.2)

- For symptomatic, documented gastroesophageal reflux and acute and recurrent diabetic gastroparesis, see Full Prescribing Information for recommended dosage reductions for elderly patients, in patients with moderate or severe hepatic or renal impairment, and cytochrome P450 2D6 (CYP2D6) poor metabolizers.

3 DOSAGE FORMS AND STRENGTHS

Tablets: 5 mg and 10 mg metoclopramide (3)

4 CONTRAINDICATIONS

- History of TD or dystonic reaction to metoclopramide (4)
- When stimulation of gastrointestinal motility might be dangerous (4)
- Pheochromocytoma, catecholamine-releasing paragangliomas (4)
- Epilepsy (4)
- Hypersensitivity to metoclopramide (4)

5 WARNINGS AND PRECAUTIONS

- Tardive Dyskinesia (TD), Other Extrapyramidal Symptoms (EPS), and Neuroleptic Malignant Syndrome (NMS): Avoid concomitant use of other drugs known to cause TD/EPS/NMS and avoid use in patients with Parkinson’s Disease. If symptoms occur, discontinue Reglan and seek immediate medical attention (5.1, 5.2, 5.3, 7.1, 7.2)
- Depression and suicidal ideation/suicide: Avoid use. (5.4)

6 ADVERSE REACTIONS

- Most common adverse reactions (> 10%) are restlessness, drowsiness, fatigue, and lassitude. (6)

To report SUSPECTED ADVERSE REACTIONS, contact ANI Pharmaceuticals, Inc. at 1-855-204-1431 or FDA at 1-800-FDA-1088 or www.fda.gov/medwatch.

7 DRUG INTERACTIONS

- Antipsychotics: Potential for additive effects, including TD, EPS, and NMS; avoid concomitant use. (7.1)
- Central Nervous System (CNS) depressants: Increased risk of CNS depression. Avoid concomitant use and monitor for adverse reactions. (7.1)
- Strong CYP2D6 inhibitors (e.g., quinidine, bupropion, fluoxetine, and paroxetine): See Full Prescribing Information for recommended dosage reductions. (2.1, 2.2, 7.1)
- Monoamine oxidase (MAO) inhibitors: Increased risk of hypertension; avoid concomitant use. (5.5, 7.1)
- Additional drug interactions: See Full Prescribing Information. (7.1, 7.2)

FULL PRESCRIBING INFORMATION

WARNING: TARDIVE DYSKINESIA

- Metoclopramide, including Reglan, can cause tardive dyskinesia (TD), a potentially irreversible serious movement disorder. In patients treated with metoclopramide, including Reglan, the risk of developing TD increases with duration of treatment and total cumulative dosage [see Warnings and Precautions (5.1)].
- Reglan is contraindicated in patients with a history of TD.
- Use Reglan for the shortest duration of treatment and periodically reassess the need for continued treatment.
- Immediately discontinue Reglan in patients who develop signs or symptoms of TD [see Warnings and Precautions (5.1)].
- In patients with symptomatic, documented gastroesophageal reflux, the maximum duration of Reglan treatment is 12 weeks [see Dosage and Administration (2.1) and Warnings and Precautions (5.1)].
- In patients with diabetic gastroparesis, avoid a total duration of treatment with metoclopramide products, including Reglan tablets, for longer than 12 weeks. If longer term use is unavoidable, routinely monitor for signs and symptoms of TD [see Warnings and Precautions (5.1)].

1 INDICATIONS AND USAGE

Reglan tablets are indicated for the:

- Treatment for 4 to 12 weeks of symptomatic, documented gastroesophageal reflux in adults who fail to respond to conventional therapy.
- Relief of symptoms in adults with acute and recurrent diabetic gastroparesis.

Limitations of Use:

- Reglan has not been shown to be safe and effective for the treatment of symptomatic, documented gastroesophageal reflux for longer than 12 weeks [see Warnings and Precautions (5.1)].
- Reglan tablets are not recommended for use in pediatric patients due to the risk of developing tardive dyskinesia (TD) and other extrapyramidal symptoms as well as the risk of methemoglobinemia in neonates [see Use in Specific Populations (8.4)].

2 DOSAGE AND ADMINISTRATION

2.1 Recommended Dosage for Symptomatic, Documented Gastroesophageal Reflux in Adults Who Fail Conventional Therapy

Reglan tablets may be administered continuously or intermittently in patients with symptomatic, documented gastroesophageal reflux who fail to respond to conventional therapy:

Continuous Dosing

- The recommended dosage of Reglan tablets is 10 to 15 mg orally four times daily. The maximum recommended daily oral dosage is 60 mg.
- Administer each dose thirty minutes before a meal and at bedtime.
- The recommended treatment duration is 4 to 12 weeks, as determined by endoscopic response. Use Reglan for the shortest duration of treatment and periodically reassess the need for continued treatment.
- The maximum recommended duration of treatment is 12 weeks [see Warnings and Precautions (5.1)].

Table 1 displays the recommended daily dosage and maximum daily dosage for adults and dosage adjustments for patients with moderate or severe hepatic impairment (Child-Pugh B or C), in patients with creatinine clearance less than 60 mL/minute, in cytochrome P450 2D6 (CYP2D6) poor metabolizers, and with concomitant use with strong CYP2D6 inhibitors.

Intermittent Dosing

If symptoms only occur intermittently or at specific times of the day, administer Reglan as a single dose up to 20 mg prior to the provoking situation. Consider dosage reductions for the populations and situations in Table 1.

Table 1. Recommended Dosage of Reglan Tablets for Symptomatic, Documented Gastroesophageal Reflux in Adults Who Fail Conventional Therapy

 | Recommended Dosage | Maximum Recommended Daily Dosage
Adult patients | 10 to 15 mg four times daily (thirty minutes before each meal and at bedtime) | 60 mg
Mild hepatic impairment (Child-Pugh A) | 10 to 15 mg four times daily (thirty minutes before each meal and at bedtime) | 60 mg
Elderly patients [see Use in Specific Populations (8.5)] | 5 mg^1 four times daily (thirty minutes before each meal and at bedtime) | 60 mg
Moderate or severe hepatic impairment (Child-Pugh B or C) [see Use in Specific Populations (8.7)] | 5 mg four times daily (thirty minutes before each meal and at bedtime), or; 10 mg taken three times daily | 30 mg
CYP2D6 poor metabolizers [see Use in Specific Populations (8.9)] | 5 mg four times daily (thirty minutes before each meal and at bedtime), or; 10 mg taken three times daily | 30 mg
Concomitant use with strong CYP2D6 inhibitors (e.g., quinidine, bupropion, fluoxetine, and paroxetine) [see Drug Interactions (7.1)] | 5 mg four times daily (thirty minutes before each meal and at bedtime), or; 10 mg taken three times daily | 30 mg
Moderate or severe renal impairment (creatinine clearance less than or equal to 60 mL/minute) [see Use in Specific Populations (8.6)] | 5 mg four times daily (thirty minutes before each meal and at bedtime), or; 10 mg taken three times daily | 30 mg
Patients with End-Stage Renal Disease (ESRD) including those treated with hemodialysis and continuous ambulatory peritoneal dialysis [see Use in Specific Populations (8.6)] | 5 mg four times daily (thirty minutes before each meal and at bedtime) or 10 mg twice daily | 20 mg

^1 Elderly patients may be more sensitive to the therapeutic or adverse effects of Reglan; therefore, consider a lower starting dosage of 5 mg four times daily with titration to the recommended adult dosage of 10 to 15 mg four times daily based upon response and tolerability.

2.2 Recommended Dosage for Acute and Recurrent Diabetic Gastroparesis in Adults

- The recommended oral dosage of Reglan tablets for the relief of symptoms in adults with acute and recurrent diabetic gastroparesis is 10 mg four times daily. The maximum recommended daily dosage is 40 mg.
- Administer each dose thirty minutes before each meal and at bedtime.
- Use Reglan for the shortest duration of treatment and periodically reassess the need for continued treatment.
- Avoid treatment with metoclopramide, including Reglan tablets, for longer than 12 weeks. If longer-term use is unavoidable, routinely monitor for signs and symptoms of TD [see Warnings and Precautions (5.1)].

Table 2 displays the recommended daily dosage and maximum daily dosage for adults and dosage adjustments for patients with moderate or severe hepatic impairment (Child-Pugh B or C), in patients with creatinine clearance less than 60 mL/minute, in cytochrome P450 2D6 (CYP2D6) poor metabolizers, and with concomitant use with strong CYP2D6 inhibitors.

If patients with diabetic gastroparesis have severe nausea or vomiting and are unable to take oral Reglan tablets, consider starting therapy with metoclopramide injection given intramuscularly or intravenously for up to 10 days (see the prescribing information for metoclopramide injection). After patients are able to take oral therapy, switch to Reglan tablets.

Table 2. Recommended Reglan Tablet Dosage in Adult Patients with Acute and Recurrent Diabetic Gastroparesis

 | Recommended Dosage | Maximum Recommended Daily Dosage
Adult Patients | 10 mg four times daily (30 minutes before each meal and at bedtime) | 40 mg
Mild hepatic impairment (Child-Pugh A) | 10 mg four times daily (30 minutes before each meal and at bedtime) | 40 mg
Elderly patients [see Use in Specific Populations (8.5)] | 5 mg^1 four times daily (30 minutes before each meal and at bedtime) | 40 mg
Moderate or severe hepatic impairment (Child-Pugh B or C) [see Use in Specific Populations (8.7)] | 5 mg four times daily (30 minutes before each meal and at bedtime) | 20 mg
CYP2D6 poor metabolizers [see Use in Specific Populations (8.9)] | 5 mg four times daily (30 minutes before each meal and at bedtime) | 20 mg
Concomitant use with strong CYP2D6 inhibitors (e.g., quinidine). Avoid use with bupropion, fluoxetine, and paroxetine [see Drug Interactions (7.1)] | 5 mg four times daily (30 minutes before each meal and at bedtime) | 20 mg
Moderate or severe renal impairment (creatinine clearance less than 60 mL/minute) [see Use in Specific Populations (8.6)] | 5 mg four times daily (30 minutes before each meal and at bedtime) | 20 mg
Patients with End-Stage Renal Disease (ESRD) including those treated with hemodialysis and continuous ambulatory peritoneal dialysis [see Use in Specific Populations (8.6)] | 5 mg twice daily | 10 mg

^1 Elderly patients may be more sensitive to the therapeutic or adverse effects of Reglan; therefore, consider a lower dosage of 5 mg four times daily with titration to the recommended adult dosage of 10 mg four times daily based upon response and tolerability.

3 DOSAGE FORMS AND STRENGTHS

Tablets:

- 5 mg metoclopramide: green, elliptical-shaped, debossed “REGLAN” over “5” on one side and “ANI” on the opposite side
- 10 mg metoclopramide: white, double edge scored, capsule-shaped, debossed “REGLAN” on one side and “ANI 10” on the opposite side

4 CONTRAINDICATIONS

Reglan is contraindicated:

- In patients with a history of tardive dyskinesia (TD) or a dystonic reaction to metoclopramide [see Warnings and Precautions (5.1, 5.2)].
- When stimulation of gastrointestinal motility might be dangerous (e.g., in the presence of gastrointestinal hemorrhage, mechanical obstruction, or perforation).
- In patients with pheochromocytoma or other catecholamine-releasing paragangliomas. Reglan may cause a hypertensive/pheochromocytoma crisis, probably due to release of catecholamines from the tumor [see Warnings and Precautions (5.5)].
- In patients with epilepsy. Reglan may increase the frequency and severity of seizures [see Adverse Reactions (6)].
- In patients with hypersensitivity to metoclopramide. Reactions have included laryngeal and glossal angioedema and bronchospasm [see Adverse Reactions (6)].

5 WARNINGS AND PRECAUTIONS

5.1 Tardive Dyskinesia

Metoclopramide, including Reglan, can cause tardive dyskinesia (TD), a syndrome of potentially irreversible and disfiguring involuntary movements of the face or tongue, and sometimes of the trunk and/or extremities. Metoclopramide, including Reglan, may also suppress, or partially suppress, the signs of TD, and may delay the diagnosis of TD because it may mask the underlying disease process. The effect of this symptomatic suppression upon the long-term course of TD is unknown. TD may remit, partially or completely, if Reglan treatment is discontinued.

In patients treated with metoclopramide, including Reglan, the risk of developing TD and the likelihood that TD will become irreversible increases with duration of treatment and total cumulative dosage. Additionally, the risk of developing TD is increased in elderly patients, especially in elderly women [see Use in Specific Populations (8.5)], and in patients with diabetes mellitus.

Prevention, Mitigation, and Monitoring for TD

- Reglan is contraindicated in patients with a history of TD.
- Avoid use of Reglan in patients receiving concomitant antipsychotics due to the potential additive effects of TD [see Drug Interactions (7.1)].
- Reduce the Reglan dosage in the elderly [see Dosage and Administration (2.1, 2.2)].
- Use Reglan for the shortest duration of treatment and periodically reassess the need for continued treatment.
- Immediately discontinue Reglan in patients who develop signs and symptoms of TD.
- In patients with symptomatic, documented gastroesophageal reflux, the maximum duration of treatment is 12 weeks [see Dosage and Administration (2.2)].
- In patients with diabetic gastroparesis, avoid a total duration of treatment with metoclopramide products, including Reglan tablets, for longer than 12 weeks. If longer-term use is unavoidable, routinely monitor for signs and symptoms of TD.
- If patients have continued TD symptoms, consider TD treatment.

5.2 Other Extrapyramidal Symptoms

In addition to TD, metoclopramide may cause other extrapyramidal symptoms (EPS), parkinsonian symptoms, and motor restlessness. Advise patients to seek immediate medical attention if such symptoms occur and to discontinue Reglan.

- Extrapyramidal symptoms (EPS), such as acute dystonic reactions, occurred in patients treated with metoclopramide dosages of 30 mg to 40 mg daily. Such reactions occurred more frequently in adults less than 30 years of age and at higher than recommended dosages. EPS occurred more frequently in pediatric patients compared to adults (Reglan is not approved for use in pediatric patients). Symptoms can occur in the first 24 to 48 hours after starting metoclopramide. Symptoms included involuntary movements of limbs and facial grimacing, torticollis, oculogyric crisis, rhythmic protrusion of tongue, bulbar type of speech, trismus, or dystonic reactions resembling tetanus. Rarely, dystonic reactions were present as stridor and dyspnea, possibly due to laryngospasm. Diphenhydramine hydrochloride or benztropine mesylate may be used to treat these adverse reactions. Avoid Reglan in patients receiving other drugs that can cause EPS (e.g., antipsychotics).
- Parkinsonian symptoms (bradykinesia, tremor, cogwheel rigidity, mask-like facies) have occurred after starting metoclopramide, more commonly within the first 6 months, but also after longer periods. Symptoms generally have subsided within 2 to 3 months after discontinuation of Reglan. Avoid Reglan in patients with Parkinson’s disease and other patients being treated with antiparkinsonian drugs due to potential exacerbation of symptoms. If treatment is unavoidable, use Reglan for the shortest duration of treatment and periodically reassess the need for continued treatment. Routinely monitor for signs and symptoms of Parkinson’s disease [see Dosage and Administration (2.1, 2.2)].
- Motor restlessness (akathisia) has developed and consisted of feelings of anxiety, agitation, jitteriness, and insomnia, as well as inability to sit still, pacing, and foot tapping. If symptoms resolve, consider restarting at a lower dosage.

5.3 Neuroleptic Malignant Syndrome

Metoclopramide may cause a potentially fatal symptom complex called neuroleptic malignant syndrome (NMS). NMS has been reported in association with metoclopramide overdosage and concomitant treatment with another drug associated with NMS. Avoid Reglan in patients receiving other drugs associated with NMS, including typical and atypical antipsychotics.

Clinical manifestations of NMS include hyperpyrexia, muscle rigidity, altered mental status, and manifestations of autonomic instability (irregular pulse or blood pressure, tachycardia, diaphoresis, and cardiac arrhythmias). Additional signs may include elevated creatine phosphokinase, myoglobinuria (rhabdomyolysis), and acute renal failure. Patients with such symptoms should be evaluated immediately.

In the diagnostic evaluation, consider the presence of other serious medical conditions (e.g., pneumonia, systemic infection) and untreated or inadequately treated extrapyramidal signs and symptoms. Other important considerations in the differential diagnosis include central anticholinergic toxicity, heat stroke, malignant hyperthermia, drug fever, serotonin syndrome, and primary central nervous system pathology.

Management of NMS includes:

- Immediate discontinuation of Reglan and other drugs not essential to concurrent therapy [see Drug Interactions (7.1)].
- Intensive symptomatic treatment and medical monitoring.
- Treatment of any concomitant serious medical problems for which specific treatments are available.

5.4 Depression

Depression has occurred in metoclopramide-treated patients with and without a history of depression. Symptoms have included suicidal ideation and suicide. Avoid Reglan use in patients with a history of depression.

5.5 Hypertension

Metoclopramide may elevate blood pressure. In one study in hypertensive patients, intravenously administered metoclopramide was shown to release catecholamines; hence, avoid use in patients with hypertension or in patients taking monoamine oxidase inhibitors [see Drug Interactions (7.1)].

There are also clinical reports of hypertensive crises in patients with undiagnosed pheochromocytoma. Reglan is contraindicated in patients with pheochromocytoma or other catecholamine-releasing paragangliomas [see Contraindications (4)]. Discontinue Reglan in any patient with a rapid rise in blood pressure.

5.6 Fluid Retention

Because Reglan produces a transient increase in plasma aldosterone, patients with cirrhosis or congestive heart failure may be at risk of developing fluid retention and volume overload. Discontinue Reglan if any of these adverse reactions occur.

5.7 Hyperprolactinemia

As with other dopamine D2 receptor antagonists, metoclopramide elevates prolactin levels.

Hyperprolactinemia may suppress hypothalamic GnRH, resulting in reduced pituitary gonadotropin secretion. This, in turn, may inhibit reproductive function by impairing gonadal steroidogenesis in both female and male patients. Galactorrhea, amenorrhea, gynecomastia, and impotence have been reported with prolactin-elevating drugs, including metoclopramide.

Hyperprolactinemia may potentially stimulate prolactin-dependent breast cancer. However, some clinical studies and epidemiology studies have not shown an association between administration of dopamine D2 receptor antagonists and tumorigenesis in humans [see Nonclinical Toxicology (13.1)].

5.8 Effects on the Ability to Drive and Operate Machinery

Metoclopramide may impair the mental and/or physical abilities required for the performance of hazardous tasks such as operating machinery or driving a motor vehicle. Concomitant use of central nervous system (CNS) depressants or drugs associated with EPS may increase this effect (e.g., alcohol, sedatives, hypnotics, opiates, and anxiolytics). Avoid Reglan or the interacting drug, depending on the importance of the drug to the patient [see Drug Interactions (7.1)].

6 ADVERSE REACTIONS

The following adverse reactions are described, or described in greater detail, in other sections of the labeling:

- Tardive dyskinesia [see Boxed Warning and Warnings and Precautions (5.1)]
- Other extrapyramidal symptoms [see Warnings and Precautions (5.2)]
- Neuroleptic malignant syndrome [see Warnings and Precautions (5.3)]
- Depression [see Warnings and Precautions (5.4)]
- Hypertension [see Warnings and Precautions (5.5)]
- Fluid retention [see Warnings and Precautions (5.6)]
- Hyperprolactinemia [see Warnings and Precautions (5.7)]
- Effects on the ability to drive and operate machinery [see Warnings and Precautions (5.8)]

The following adverse reactions have been identified from clinical studies or postmarketing reports of metoclopramide. Because these reactions are reported voluntarily from a population of uncertain size, it is not always possible to reliably estimate their frequency or establish a causal relationship to drug exposure.

The most common adverse reactions (in approximately 10% of patients receiving 10 mg of metoclopramide four times daily) were restlessness, drowsiness, fatigue, and lassitude. In general, the incidence of adverse reactions correlated with the dosage and duration of metoclopramide administration.

Adverse reactions, especially those involving the nervous system, occurred after stopping metoclopramide including dizziness, nervousness, and headaches.

Central Nervous System Disorders

- Tardive dyskinesia, acute dystonic reactions, drug-induced parkinsonism, akathisia, and other extrapyramidal symptoms
- Convulsive seizures
- Hallucinations
- Restlessness, drowsiness, fatigue, and lassitude occurred in approximately 10% of patients who received 10 mg four times daily. Insomnia, headache, confusion, dizziness, or depression with suicidal ideation occurred less frequently.
- Neuroleptic malignant syndrome, serotonin syndrome (in combination with serotonergic agents).

Endocrine Disorders: Fluid retention secondary to transient elevation of aldosterone. Galactorrhea, amenorrhea, gynecomastia, impotence secondary to hyperprolactinemia

Cardiovascular Disorders: Acute congestive heart failure, possible atrioventricular block, hypotension, hypertension, supraventricular tachycardia, bradycardia, fluid retention

Gastrointestinal Disorders: Nausea, bowel disturbances (primarily diarrhea)

Hepatic Disorders: Hepatotoxicity, characterized by, e.g., jaundice and altered liver function tests, when metoclopramide was administered with other drugs with known hepatotoxic potential

Renal and Urinary Disorders: Urinary frequency, urinary incontinence

Hematologic Disorders: Agranulocytosis, neutropenia, leukopenia, methemoglobinemia, sulfhemoglobinemia

Hypersensitivity Reactions: Bronchospasm (especially in patients with a history of asthma), urticaria; rash; angioedema, including glossal or laryngeal edema

Eye Disorders: Visual disturbances

Metabolism Disorders: Porphyria

7 DRUG INTERACTIONS

7.1 Effects of Other Drugs on Metoclopramide

Table 3 displays the effects of other drugs on metoclopramide.

Table 3. Effects of Other Drugs on Metoclopramide

Antipsychotics
Clinical Impact | Potential for additive effects, including increased frequency and severity of tardive dyskinesia (TD), other extrapyramidal symptoms (EPS), and neuroleptic malignant syndrome (NMS).
Intervention | Avoid concomitant use [see Warnings and Precautions (5.1, 5.2, 5.3)].
Strong CYP2D6 Inhibitors, not Included in Antipsychotic Category Above
Clinical Impact | Increased plasma concentrations of metoclopramide; risk of exacerbation of extrapyramidal symptoms [see Clinical Pharmacology (12.3)].
Intervention | Reduce the Reglan dosage [see Dosage and Administration (2.1, 2.2)].
Examples | quinidine, bupropion, fluoxetine, and paroxetine
Monoamine Oxidase Inhibitors
Clinical Impact | Increased risk of hypertension [see Warnings and Precautions (5.5)].
Intervention | Avoid concomitant use.
Central Nervous System (CNS) Depressants
Clinical Impact | Increased risk of CNS depression [see Warnings and Precautions (5.8)].
Intervention | Avoid Reglan or the interacting drug, depending on the importance of the drug to the patient.
Examples | alcohol, sedatives, hypnotics, opiates and anxiolytics
Drugs that Impair Gastrointestinal Motility
Clinical Impact | Decreased systemic absorption of metoclopramide.
Intervention | Monitor for reduced therapeutic effect.
Examples | antiperistaltic antidiarrheal drugs, anticholinergic drugs, and opiates
Dopaminergic Agonists and Other Drugs that Increase Dopamine Concentrations
Clinical Impact | Decreased therapeutic effect of metoclopramide due to opposing effects on dopamine.
Intervention | Monitor for reduced therapeutic effect.
Examples | apomorphine, bromocriptine, cabergoline, levodopa, pramipexole, ropinirole, and rotigotine

7.2 Effects of Metoclopramide on Other Drugs

Table 4 displays the effects of metoclopramide on other drugs.

Table 4. Effects of Metoclopramide on Other Drugs

Dopaminergic Agonists and Drugs Increasing Dopamine Concentrations
Clinical Impact | Opposing effects of metoclopramide and the interacting drug on dopamine. Potential exacerbation of symptoms (e.g., parkinsonian symptoms).
Intervention | Avoid concomitant use [see Warnings and Precautions (5.2)].
Examples | Apomorphine, bromocriptine, cabergoline, levodopa, pramipexole, ropinirole, rotigotine
Succinylcholine, Mivacurium
Clinical Impact | Metoclopramide inhibits plasma cholinesterase leading to enhanced neuromuscular blockade.
Intervention | Monitor for signs and symptoms of prolonged neuromuscular blockade.
Drugs with Absorption Altered due to Increased Gastrointestinal Motility
Clinical Impact | The effect of metoclopramide on other drugs is variable. Increased gastrointestinal (GI) motility by metoclopramide may impact absorption of other drugs leading to decreased or increased drug exposure.
Intervention | Drugs with Decreased Absorption (e.g., digoxin, atovaquone, posaconazole oral suspension*, fosfomycin): Monitor for reduced therapeutic effect of the interacting drug. For digoxin monitor therapeutic drug concentrations and increase the digoxin dose as needed (see prescribing information for digoxin).; Drugs with Increased Absorption (e.g., sirolimus, tacrolimus, cyclosporine): Monitor therapeutic drug concentrations and adjust the dose as needed. See prescribing information for the interacting drug.
Insulin
Clinical Impact | Increased GI motility by metoclopramide may increase delivery of food to the intestines and increase blood glucose.
Intervention | Monitor blood glucose and adjust insulin dosage regimen as needed.

* Interaction does not apply to posaconazole delayed-release tablets

8 USE IN SPECIFIC POPULATIONS

8.1 Pregnancy

Risk Summary

Published studies, including retrospective cohort studies, national registry studies, and meta-analyses, do not report an increased risk of adverse pregnancy-related outcomes with use of metoclopramide during pregnancy.

There are potential risks to the neonate following exposure in utero to metoclopramide during delivery (see Clinical Considerations). In animal reproduction studies, no adverse developmental effects were observed with oral administration of metoclopramide to pregnant rats and rabbits at exposures about 6 and 12 times the maximum recommended human dose (MRHD) (see Data).

The background risk of major birth defects and miscarriage for the indicated population is unknown. All pregnancies have a background risk of birth defects, loss or other adverse outcomes. In the U.S. general population, the estimated background risk of major birth defects and miscarriage in the clinically recognized pregnancies is 2 to 4% and 15 to 20%, respectively.

Clinical Considerations

Fetal/Neonatal Adverse Reactions

Metoclopramide crosses the placental barrier and may cause extrapyramidal signs and methemoglobinemia in neonates with maternal administration during delivery. Monitor neonates for extrapyramidal signs [see Warnings and Precautions (5.1, 5.2), Use in Specific Populations (8.4)].

Data

Animal Data

Reproduction studies have been performed following administration of oral metoclopramide during organogenesis in pregnant rats at about 6 times the MRHD calculated on body surface area and in pregnant rabbits at about 12 times the MRHD calculated on body surface area. No evidence of adverse developmental effects due to metoclopramide were observed.

8.2 Lactation

Risk Summary

Limited published data report the presence of metoclopramide in human milk in variable amounts (see Data). Breastfed infants exposed to metoclopramide have experienced gastrointestinal adverse reactions, including intestinal discomfort and increased intestinal gas formation (see Clinical Considerations). Metoclopramide elevates prolactin levels [see Warnings and Precautions (5.7)]; however, the published data are not adequate to support drug effects on milk production. The developmental and health benefits of breastfeeding should be considered along with the mother’s clinical need for Reglan and any potential adverse effects on the breastfed child from Reglan or from the underlying maternal condition.

Clinical Considerations

Monitor breastfeeding neonates because metoclopramide may cause extrapyramidal signs (dystonias) and methemoglobinemia [see Warnings and Precautions (5.1, 5.2), Use in Specific Populations (8.4)].

Data

In published clinical studies, the estimated amount of metoclopramide received by the breastfed infant was less than 10% of the maternal weight-adjusted dose. In one study, the estimated daily amount of metoclopramide received by infants from breast milk ranged from 6 to 24 mcg/kg/day in early puerperium (3 to 9 days postpartum) and from 1 to 13 mcg/kg/day at 8 to 12 weeks postpartum.

8.4 Pediatric Use

Metoclopramide is not recommended for use in pediatric patients due to the risk of tardive dyskinesia (TD) and other extrapyramidal symptoms as well as the risk of methemoglobinemia in neonates. The safety and effectiveness of Reglan tablets in pediatric patients have not been established.

Dystonias and other extrapyramidal symptoms associated with metoclopramide are more common in pediatric patients than in adults [see Warnings and Precautions (5.1, 5.2)]. In addition, neonates have reduced levels of NADH-cytochrome b5 reductase, making them more susceptible to methemoglobinemia, a possible adverse reaction of metoclopramide use in neonates [see Use in Specific Populations (8.8)].

8.5 Geriatric Use

Metoclopramide is known to be substantially excreted by the kidney, and the risk of adverse reactions, including tardive dyskinesia (TD), may be greater in patients with impaired renal function [see Use in Specific Populations (8.6), Clinical Pharmacology (12.3)]. Elderly patients are more likely to have decreased renal function and may be more sensitive to the therapeutic or adverse effects of metoclopramide; therefore, consider a reduced dosage of Reglan in elderly patients [see Boxed Warning, Dosage and Administration (2.1, 2.2), Warnings and Precautions (5.1)].

8.6 Renal Impairment

The clearance of metoclopramide is decreased and the systemic exposure is increased in patients with moderate to severe renal impairment compared to patients with normal renal function, which may increase the risk of adverse reactions. Reduce the Reglan dosage in patients with moderate and severe renal impairment (creatinine clearance less than or equal to 60 mL/minute), including those receiving hemodialysis and continuous ambulatory peritoneal dialysis [see Dosage and Administration (2.1, 2.2), Clinical Pharmacology (12.3)].

8.7 Hepatic Impairment

Patients with severe hepatic impairment (Child-Pugh C) have reduced systemic metoclopramide clearance (by approximately 50%) compared to patients with normal hepatic function. The resulting increase in metoclopramide blood concentrations increases the risk of adverse reactions. There is no pharmacokinetic data in patients with moderate hepatic impairment (Child-Pugh B). Reduce the Reglan dosage in patients with moderate or severe (Child-Pugh B or C) hepatic impairment [see Dosage and Administration (2.1, 2.2)]. There is no dosage adjustment required for patients with mild hepatic impairment (Child-Pugh A).

Metoclopramide, by producing a transient increase in plasma aldosterone, may increase the risk of fluid retention in patients with hepatic impairment [see Warnings and Precautions (5.6)].

Monitor patients with hepatic impairment for the occurrence of fluid retention and volume overload.

8.8 NADH-Cytochrome b5 Reductase Deficiency

Metoclopramide-treated patients with NADH-cytochrome b5 reductase deficiency are at an increased risk of developing methemoglobinemia and/or sulfhemoglobinemia. For patients with glucose-6-phosphate dehydrogenase (G6PD) deficiency with metoclopramide-induced methemoglobinemia, methylene blue treatment is not recommended. Methylene blue may cause hemolytic anemia in patients with G6PD deficiency, which may be fatal [see Overdosage (10)].

8.9 CYP2D6 Poor Metabolizers

Metoclopramide is a substrate of CYP2D6. The elimination of metoclopramide may be slowed in patients who are CYP2D6 poor metabolizers (compared to patients who are CYP2D6 intermediate, extensive, or ultra-rapid metabolizers); possibly increasing the risk of dystonic and other adverse reactions to Reglan [see Clinical Pharmacology (12.3)]. Reduce the Reglan dosage in patients who are poor CYP2D6 metabolizers [see Dosage and Administration (2.1, 2.2)].

10 OVERDOSAGE

Manifestations of metoclopramide overdosage included drowsiness, disorientation, extrapyramidal reactions, other adverse reactions associated with metoclopramide use (including, e.g., methemoglobinemia), and sometimes death. Neuroleptic malignant syndrome (NMS) has been reported in association with metoclopramide overdose and concomitant treatment with another drug associated with NMS [see Warnings and Precautions (5.1, 5.2, 5.3)].

There are no specific antidotes for Reglan overdosage. If over-exposure occurs, call your Poison Control Center at 1-800-222-1222 for current information on the management of poisoning or overdosage.

Methemoglobinemia can be reversed by the intravenous administration of methylene blue. However, methylene blue may cause hemolytic anemia in patients with glucose-6-phosphate dehydrogenase (G6PD) deficiency, which may be fatal.

Hemodialysis and continuous ambulatory peritoneal dialysis do not remove significant amounts of metoclopramide.

11 DESCRIPTION

Metoclopramide hydrochloride, the active ingredient of Reglan, is a dopamine-2 receptor antagonist. Metoclopramide hydrochloride (metoclopramide monohydrochloride monohydrate) is a white crystalline, odorless substance, freely soluble in water. Its chemical name is 4-amino-5-chloro-N-[2-(diethylamino)ethyl]-2-methoxy benzamide monohydrochloride monohydrate.

The molecular formula is C14H22ClN3O2•HCl•H2O. Its molecular weight is 354.3. The structural formula is:

Reglan tablets are for oral administration. Reglan is available in 5 mg and 10 mg tablets.

- Each Reglan 5 mg tablet contains 5 mg metoclopramide (equivalent to 5.91 mg of metoclopramide hydrochloride USP). Inactive ingredients consist of corn starch, D&C Yellow 10 Aluminum Lake, FD&C Blue 1 Aluminum Lake, lactose, microcrystalline cellulose, silicon dioxide, and stearic acid.
- Each Reglan 10 mg tablet contains 10 mg metoclopramide (equivalent to 11.82 mg metoclopramide hydrochloride USP). Inactive ingredients consist of magnesium stearate, mannitol, microcrystalline cellulose, and stearic acid.

12 CLINICAL PHARMACOLOGY

12.1 Mechanism of Action

Metoclopramide stimulates motility of the upper gastrointestinal tract without stimulating gastric, biliary, or pancreatic secretions. The exact mechanism of action of metoclopramide in the treatment of gastroesophageal reflux and acute and recurrent diabetic gastroparesis has not been fully established. It seems to sensitize tissues to the action of acetylcholine. The effect of metoclopramide on motility is not dependent on intact vagal innervation, but it can be abolished by anticholinergic drugs.

Metoclopramide increases the tone and amplitude of gastric (especially antral) contractions, relaxes the pyloric sphincter and the duodenal bulb, and increases peristalsis of the duodenum and jejunum resulting in accelerated gastric emptying and intestinal transit. It increases the resting tone of the lower esophageal sphincter. It has little, if any, effect on the motility of the colon or gallbladder.

12.2 Pharmacodynamics

Gastroesophageal Reflux

In patients with gastroesophageal reflux and low lower esophageal sphincter pressure (LESP), single oral doses of Reglan produced dose-related increases in LESP. Effects began at about 5 mg and increased through 20 mg. The increase in LESP from a 5 mg dose lasted about 45 minutes and that of 20 mg lasted between 2 and 3 hours. Increased rate of stomach emptying was observed with single oral doses of 10 mg.

12.3 Pharmacokinetics

Absorption

Relative to an intravenous dose of 20 mg, the absolute bioavailability of oral metoclopramide is 80% ± 15.5% as demonstrated in a crossover study of 18 subjects. Peak plasma concentrations occurred at about 1 to 2 hours after a single oral dose. Similar time to peak was observed after individual doses at steady state.

In a single dose study of 12 subjects, the area under the drug concentration-time curve increased linearly with doses from 20 to 100 mg (5 times the maximum recommended single dose). Peak concentrations increased linearly with dose; time to peak concentrations remained the same; whole body clearance was unchanged; and the elimination rate remained the same. The mean elimination half-life in subjects with normal renal function was 5 to 6 hours. Linear kinetic processes adequately describe the absorption and elimination of metoclopramide.

Distribution

Metoclopramide is not extensively bound to plasma proteins (about 30%). The whole body volume of distribution is high (about 3.5 L/kg), which suggests extensive distribution of drug to the tissues.

Elimination

Metabolism: Metoclopramide undergoes enzymatic metabolism via oxidation as well as glucuronide and sulfate conjugation reactions in the liver. Monodeethylmetoclopramide, a major oxidative metabolite, is formed primarily by CYP2D6, an enzyme subject to genetic variability [see Dosage and Administration (2.1, 2.2), Use in Specific Populations (8.9)].
Excretion: Approximately 85% of the radioactivity of an orally administered dose appeared in the urine within 72 hours. After oral administration of 10 or 20 mg, a mean of 18% and 22% of the dose, respectively, was recovered as free metoclopramide in urine within 36 hours.

Specific Populations

Patients with Renal Impairment: In a study of 24 patients with varying degrees of renal impairment (moderate, severe, and end-stage renal disease (ESRD) requiring dialysis), the systemic exposure (AUC) of metoclopramide in patients with moderate to severe renal impairment was about 2-fold the AUC in subjects with normal renal function. The AUC of metoclopramide in patients with ESRD on dialysis was about 3.5-fold the AUC in subjects with normal renal function [see Dosage and Administration (2.1, 2.2) and Use in Specific Populations (8.6)].
Patients with Hepatic Impairment: In a group of 8 patients with severe hepatic impairment (Child-Pugh C), the average metoclopramide clearance was reduced by approximately 50% compared to patients with normal hepatic function [see Dosage and Administration (2.1, 2.2) and Use in Specific Populations (8.7)].

Drug Interaction Studies

Effect of Metoclopramide on CYP2D6 Substrates
Although in vitro studies suggest that metoclopramide can inhibit CYP2D6, metoclopramide is unlikely to interact with CYP2D6 substrates in vivo at therapeutically relevant concentrations.
Effect of CYP2D6 Inhibitors on Metoclopramide
In healthy subjects, 20 mg of metoclopramide and 60 mg of fluoxetine (a strong CYP2D6 inhibitor) were administered, following prior exposure to 60 mg fluoxetine orally for 8 days. The patients who received concomitant metoclopramide and fluoxetine had a 40% and 90% increase in metoclopramide Cmax and AUC0-∞, respectively, compared to patients who received metoclopramide alone (see Table 5) [see Drug Interactions (7.1)].

Table 5. Metoclopramide Pharmacokinetic Parameters in Healthy Subjects with and without Fluoxetine

Parameter | Metoclopramide alone; (mean ± SD) | Metoclopramide with fluoxetine; (mean ± SD)
Cmax (ng/mL) | 44 ±15 | 62.7 ± 9.2
AUC0-∞ (ngˑh/mL) | 313 ± 113 | 591 ± 140
t1/2 (h) | 5.5 ± 1.1 | 8.5 ± 2.2

13 NONCLINICAL TOXICOLOGY

13.1 Carcinogenesis, Mutagenesis, Impairment of Fertility

Carcinogenesis

A 77-week study was conducted in rats with oral metoclopramide doses up to 40 mg/kg/day (about six times the maximum recommended human dose on body surface area basis). Metoclopramide elevated prolactin levels and the elevation persisted during chronic administration. An increase in mammary neoplasms was found in rodents after chronic administration of metoclopramide [see Warnings and Precautions (5.7)]. In a rat model for assessing the tumor promotion potential, a 2-week oral treatment with metoclopramide at a dose of 260 mg/kg/day (about 35 times the maximum recommended human dose based on body surface area) enhanced the tumorigenic effect of N-nitrosodiethylamine.

Mutagenesis

Metoclopramide was positive in the in vitro Chinese hamster lung cell/HGPRT forward mutation assay for mutagenic effects and in the in vitro human lymphocyte chromosome aberration assay for clastogenic effects. It was negative in the in vitro Ames mutation assay, the in vitro unscheduled DNA synthesis assay with rat and human hepatocytes, and the in vivo rat micronucleus assay.

Impairment of Fertility

Metoclopramide at intramuscular doses up to 20 mg/kg/day (about three times the maximum recommended human dose based on body surface area) was found to have no effect on fertility and reproductive performance of male and female rats.

16 HOW SUPPLIED/STORAGE AND HANDLING

Each green, elliptical-shaped Reglan tablet contains 5 mg metoclopramide. The tablet is debossed “REGLAN” over “5” on one side and “ANI” on the opposite side. Available in bottles of 100 tablets (NDC 62559-165-01)

Each white, double edge scored, capsule-shaped Reglan tablet contains 10 mg metoclopramide. The tablet is debossed “REGLAN” on one side and “ANI 10” on the opposite side. Available in bottles of 100 tablets (NDC 62559-166-01)

Dispense tablets in tight, light-resistant container. Store tablets at controlled room temperature between 20°C and 25°C (68°F and 77°F).

17 PATIENT COUNSELING INFORMATION

Advise the patient to read the FDA-approved patient labeling (Medication Guide).

Tardive Dyskinesia and/or other Extrapyramidal Reactions

Inform patients that Reglan may cause tardive dyskinesia or other extrapyramidal symptoms, parkinsonian symptoms, and motor restlessness. Instruct patients to immediately discontinue Reglan and contact their healthcare provider if symptoms occur [see Warnings and Precautions (5.1, 5.2)].

Neuroleptic Malignant Syndrome

Inform patients that serious neuroleptic malignant syndrome (NMS) has been reported in association with concomitant treatment with another drug associated with NMS. Advise patients to report all prescription and over-the-counter medications to the healthcare provider. Instruct patients to immediately discontinue Reglan and seek medical attention if symptoms occur [see Warnings and Precautions (5.3)].

Depression and/or Possible Suicidal Ideation

Inform patients that symptoms of new onset or worsening depression as well as suicidal ideation have been reported in patients taking metoclopramide. Instruct patients to immediately discontinue Reglan and contact their healthcare provider if any of these symptoms occur [see Warnings and Precautions (5.4)].

Drug Interactions

Inform patients or their caregivers that concomitant treatment with numerous other medications can precipitate or worsen serious adverse reactions such as tardive dyskinesia or other extrapyramidal reactions, neuroleptic malignant syndrome, and CNS depression [see Drug Interactions (7.1, 7.2)]. Explain that the prescriber of any other medication must be made aware that the patient is taking Reglan.

Effects on the Ability to Drive and Operate Machinery

Inform patients or their caregivers that Reglan can cause drowsiness or dizziness, or otherwise impair the mental and/or physical abilities required for the performance of hazardous tasks such as operating machinery or driving a motor vehicle [see Warnings and Precautions (5.8)].

Manufactured by:
ANI Pharmaceuticals, Inc.
Baudette, MN 56623

Medication Guide

REGLAN® (REG-lan)
(metoclopramide) tablets, oral use

Read this Medication Guide before you start taking REGLAN and each time you get a refill. There may be new information. If you take another product that contains metoclopramide (such as REGLAN injection, metoclopramide orally disintegrating tablets, or metoclopramide oral solution), you should read the Medication Guide that comes with that product. Some of the information may be different. This information does not take the place of talking with your healthcare provider about your medical condition or your treatment.

What is the most important information I should know about REGLAN?

REGLAN can cause a potentially irreversible serious side effect called tardive dyskinesia (abnormal muscle movements).

- These movements happen mostly in the face or tongue, and sometimes in other body parts. You cannot control these movements.
- These symptoms may not go away even after stopping REGLAN.

Your chances of getting tardive dyskinesia increase:

- the longer you take REGLAN and the more REGLAN you take.
  - Use the lowest dose possible for the shortest time needed.
  - People taking REGLAN to relieve heartburn symptoms with gastroesophageal reflux should not take REGLAN for more than 12 weeks.
  - People taking REGLAN to relieve symptoms of slow stomach emptying due to diabetes, should not take REGLAN for more than 12 weeks. If you require treatment for longer than 12 weeks, your healthcare provider should frequently monitor you for signs and symptoms of tardive dyskinesia.
- if you are older, especially if you are an older woman.
- if you have diabetes.

It is not possible for your healthcare provider to know if you will get tardive dyskinesia if you take REGLAN.

Stop taking REGLAN and call your healthcare provider right away if you get movements you cannot stop or control, such as:

- lip smacking, chewing, or puckering up your mouth
- frowning or scowling
- sticking out your tongue
- blinking and moving your eyes
- shaking of your arms and legs

Your healthcare provider may decide not to continue treatment with REGLAN if you develop signs or symptoms of tardive dyskinesia

See the section "What are the possible side effects of REGLAN?" for more information about side effects.

What is REGLAN?

REGLAN is a prescription medicine used in adults:

- for 4 to 12 weeks to relieve heartburn symptoms with gastroesophageal reflux when certain other treatments do not work.
- to relieve the symptoms of slow stomach emptying in people with diabetes.

REGLAN is not recommended for use in children or for longer than 12 weeks if you are being treated to relieve heart burn symptoms with gastroesophageal reflux.

Do not take REGLAN if you:

- have a history of tardive dyskinesia or have a problem controlling your muscles and movements after taking REGLAN or a medicine that works like REGLAN.
- have stomach or intestine problems that could get worse with REGLAN, such as bleeding, blockage or a tear in the stomach or bowel wall.
- have a type of tumor that can cause high blood pressure such as pheochromocytoma.
- have epilepsy (seizures). REGLAN can increase your chance for seizures and make them worse.
- are allergic to metoclopramide. REGLAN can cause serious allergic reactions. Stop taking REGLAN right away and get emergency help if you have any of these symptoms:
  - swelling of your tongue, throat, lips, eyes or face.
  - trouble swallowing or breathing.
  - skin rash, hives, sores in your mouth, or skin blisters.

Before taking REGLAN, tell your healthcare provider about all of your medical conditions, including if you:

- had problems controlling your muscle movements after taking any medicine.
- have Parkinson’s disease.
- have or had depression or mental illness.
- have kidney or liver disease.
- have heart failure or heart rhythm problems.
- have high blood pressure.
- drink alcohol.
- have diabetes. Your dose of insulin may need to be changed.
- are pregnant or plan to become pregnant. REGLAN may harm your unborn baby if taken during the end of pregnancy. Talk to your healthcare provider if you become pregnant while taking REGLAN.
- are breastfeeding or plan to breastfeed. REGLAN can pass into your breast milk and may harm your baby. You and your healthcare provider should decide if you will take REGLAN or breastfeed.

Tell your healthcare provider about all the medicines you take, including prescription and over-the-counter medicines, vitamins, and herbal supplements.

REGLAN may affect the way other medicines work, and other medicines may affect how REGLAN works.

Tell your healthcare provider before you start or stop other medicines.

Especially tell your healthcare provider if you take:

- another medicine that contains metoclopramide, such as metoclopramide injection, or metoclopramide orally disintegrating tablets (ODT), metoclopramide oral solution, or Gimoti nasal spray
- an anti-psychotic medicine, used to treat mental illness such as schizophrenia
- a medicine for Parkinson’s disease
- a medicine for depression, especially a Monoamine Oxidase Inhibitor (MAOI)
- insulin
- medicines that can make you sleepy, such as anti-anxiety medicines, sleep medicines, and narcotics

If you are not sure if your medicine is one listed above, ask your healthcare provider or pharmacist.

Know the medicines you take. Keep a list of them to show your healthcare provider and pharmacist when you get a new medicine.

How should I take REGLAN?

- Take REGLAN exactly as your healthcare provider tells you. Do not change your dose unless your healthcare provider tells you to.
- REGLAN comes as a tablet you take by mouth.
- Take REGLAN at least 30 minutes before each meal and at bedtime.
- You should not take medicines containing metoclopramide (including REGLAN) for more than 12 weeks.
  - If you are being treated with REGLAN to relieve the symptoms of slow stomach emptying due to diabetes and require treatment for longer than 12 weeks, your healthcare provider should frequently monitor you for signs and symptoms of tardive dyskinesia.
- If you take too much REGLAN, call your poison control center at 1-800-222-1222 or go to the nearest emergency room right away.
- Keep all follow-up visits with your healthcare provider as scheduled, so that your healthcare provider can see how you are responding to treatment with REGLAN.

What should I avoid while taking REGLAN?

- Do not drink alcohol while taking REGLAN. Alcohol may make some side effects of REGLAN worse, such as feeling sleepy.
- Do not drive, operate machinery, or do other dangerous activities until you know how REGLAN affects you. REGLAN may cause sleepiness or dizziness.

What are the possible side effects of REGLAN?

- Tardive dyskinesia (abnormal muscle movements). See “What is the most important information I need to know about REGLAN?”
- Other changes in muscle control and movement, such as:
  - Uncontrolled spasms of your face and neck muscles, or muscles of your body, arms, and legs (dystonia). These muscle spasms can cause abnormal movements and body positions, and speech problems. These spasms usually start within the first 2 days of treatment. Rarely, these muscle spasms may cause trouble breathing. These spasms happen more often in adults less than 30 years of age who took higher doses of REGLAN.
  - Parkinsonism. Symptoms include slight shaking, body stiffness, trouble moving or keeping your balance. If you already have Parkinson's Disease, your symptoms may become worse while you are taking REGLAN.
  - Being unable to sit still or feeling you need to move your hands, feet, or body (akathisia). Symptoms can include feeling jittery, anxious, irritated or unable to sleep (insomnia), feeling the need to walk around (pacing) and tapping your feet.
- Neuroleptic Malignant Syndrome (NMS). NMS is a very rare but very serious condition that can happen with REGLAN. NMS can cause death and must be treated in a hospital. Symptoms of NMS include: high fever, stiff muscles, problems thinking, very fast or uneven heartbeat, and increased sweating.
- Depression, thoughts about suicide, and suicide. Some people who take REGLAN become depressed, even if they have no history of despression. You may have thoughts about hurting or killing yourself. Some people who have taken REGLAN have ended their own lives (suicide).
- High blood pressure. REGLAN can cause your blood pressure to increase.
- Too much body water. People who have certain liver problems or heart failure and take REGLAN may hold too much water in their body (fluid retention). Tell your doctor right away if you have sudden weight gain, or swelling of your hands, legs, or feet.
- Increased prolactin. Tell your doctor if your menstrual periods stop, your breasts get larger and make milk, or you cannot have sex (impotence). These symptoms go away when you stop taking REGLAN.

Stop taking REGLAN, call your healthcare provider and get medical help right away if you:

- have muscle movements you cannot stop or control
- have muscle movements that are new or unusual
- feel depressed or have thoughts about hurting or killing yourself
- have high fever, stiff muscles, problems thinking, very fast or uneven heartbeat, and increased sweating

The most common side effects of REGLAN include:

- restlessness
- drowsiness
- tiredness
- lack of energy

You may have more side effects the longer you take REGLAN and the more REGLAN you take.

You may still have side effects after stopping REGLAN. You may have symptoms from stopping REGLAN such as headaches and feeling dizzy or nervous.

Tell your healthcare provider about any side effect that bothers you or that does not go away. These are not all the possible side effects of REGLAN. Call your doctor for medical advice about side effects. You may report side effects to FDA at 1-800-FDA-1088.

How should I store REGLAN?

- Store REGLAN at room temperature between 68°F to 77°F (20°C to 25°C).
- Keep REGLAN in the bottle it comes in and away from light. Keep the bottle closed tightly.

Keep REGLAN and all medicines out of the reach of children.

General information about the safe and effective use of REGLAN.

Medicines are sometimes prescribed for purposes other than those listed in a Medication Guide. Do not use REGLAN for a condition for which it was not prescribed. Do not give REGLAN to other people, even if they have the same symptoms that you have. It may harm them.

You can ask your pharmacist or healthcare provider for information about REGLAN that is written for health professionals.

What are the ingredients in REGLAN?

Active ingredient: metoclopramide

Inactive ingredients:

REGLAN 5 mg tablets: corn starch, D&C yellow 10 aluminum lake, FD&C blue 1 aluminum lake, lactose, microcrystalline cellulose, silicon dioxide, stearic acid

REGLAN 10 mg tablets: magnesium stearate, mannitol, microcrystalline cellulose, stearic acid

Manufactured by: ANI Pharmaceuticals, Inc., Baudette, MN 56623
For more information, go to www.anipharmaceuticals.com or call 1-855-204-1431.

This Medication Guide has been approved by the U.S. Food and Drug Administration.
Revised: February 2026

PACKAGE/LABEL PRINCIPAL DISPLAY PANEL

Reglan® (metoclopramide) Tablets USP, 5 mg
NDC 62559-165-01
Rx only
100 Tablets

PACKAGE/LABEL PRINCIPAL DISPLAY PANEL

Reglan® (metoclopramide) Tablets USP, 10 mg
NDC 62559-166-01
Rx only
100 Tablets